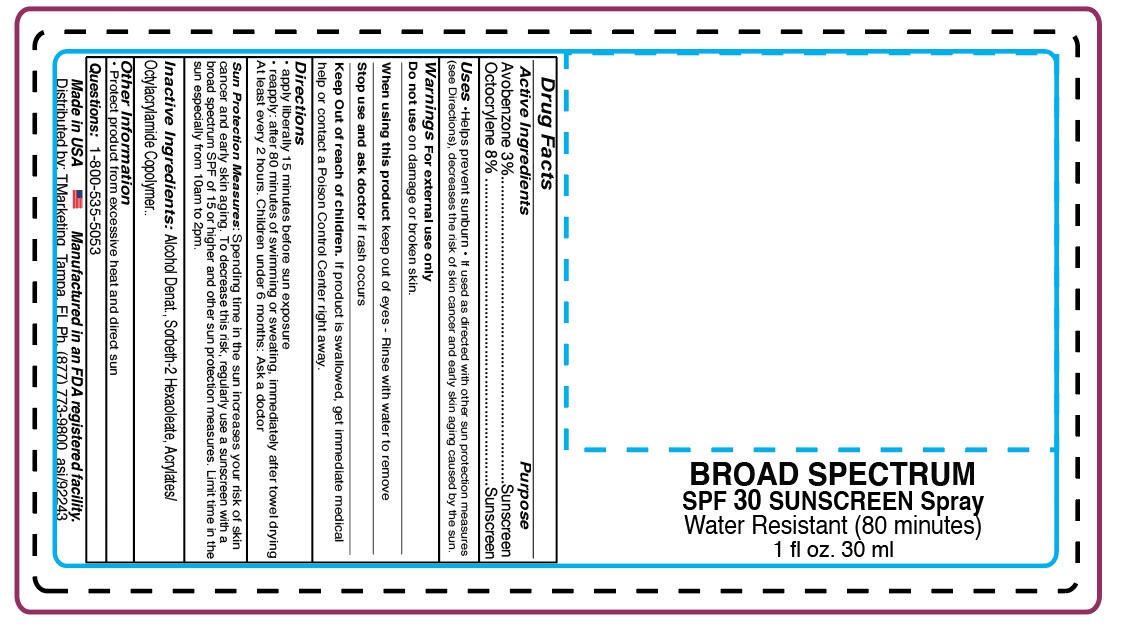 DRUG LABEL: SS-TMPFL
NDC: 58418-001 | Form: SPRAY
Manufacturer: Tropical Enterprises International, Inc.
Category: otc | Type: HUMAN OTC DRUG LABEL
Date: 20200308

ACTIVE INGREDIENTS: OCTOCRYLENE 1.98 g/30 mL; AVOBENZONE 0.7425 g/30 mL
INACTIVE INGREDIENTS: ACRYLATE/ISOBUTYL METHACRYLATE/N-TERT-OCTYLACRYLAMIDE COPOLYMER (75000 MW); SORBETH-12 HEXAOLEATE; ALCOHOL

SPF30 BROAD SPECTRUM SPRAY
FORMULA #SS-TMPFL

DOSAGE AND ADMINISTRATION

Directions: Apply liberally and evenly 15 minutes before sun exposure. Reapply after 80 minutes of swimming or sweating, immediately after towel drying, AND at least every 2 hours.

80mn update

Apply liberally and evenly 15 minutes before sun exposure.

Reapply after 80 minutes of swimming or sweating, immediately after

towel drying AND at least every 2 hours.

INACTIVE INGREDIENT

Inactive Ingredients: Alcohol Denatured, Sorbeth-2 Hexaoleate, Acrylates/, Octylacrylamide Copolymer

Other Information:

Protect product from excessive heat and direct sun.

Keep out of reach of children. If product is swallowed seek immediate medical attention or contact a Poison Control Center right away.

Purpose: Sunscreen

WARNINGS

WARNINGS: Skin Cancer/Skin Aging Alert: Spending time in the sun increases your risk of skin cancer and early skin aging. This product has been shown only to prevent sunburn not skin cancer and early skin aging.

For external use only.

When using this product avoid contact with eyes. If contact with eyes occurs, flush with water to remove.

Stop use and ask a doctor if irritation or rash develops and persists.

Active Ingredients

Avobenzone 3%

Octocrylene 8%

Questions? Call